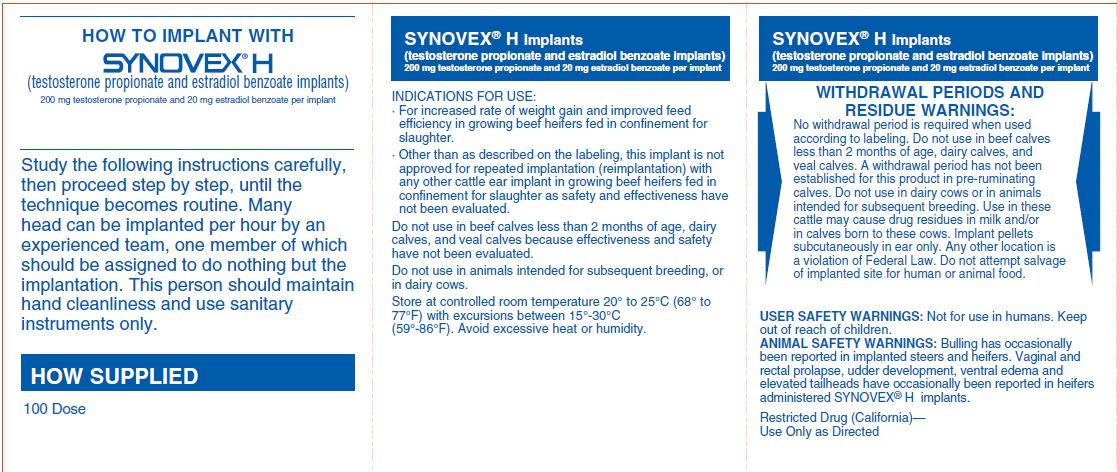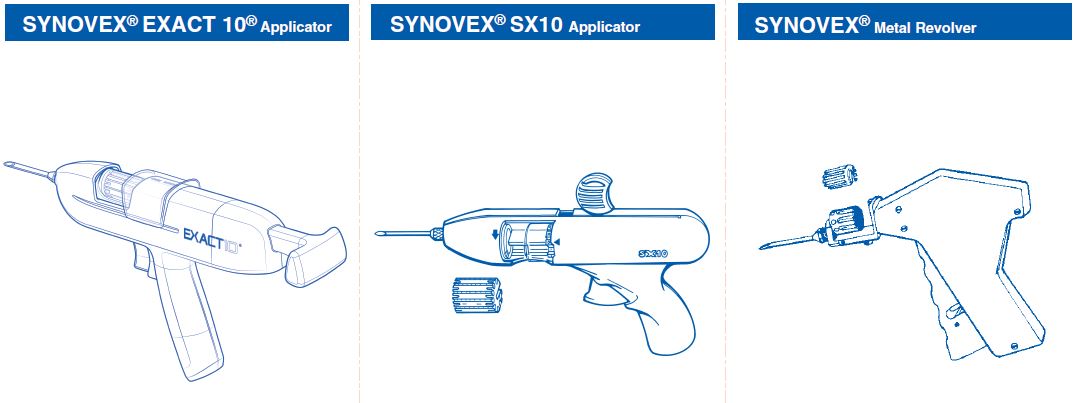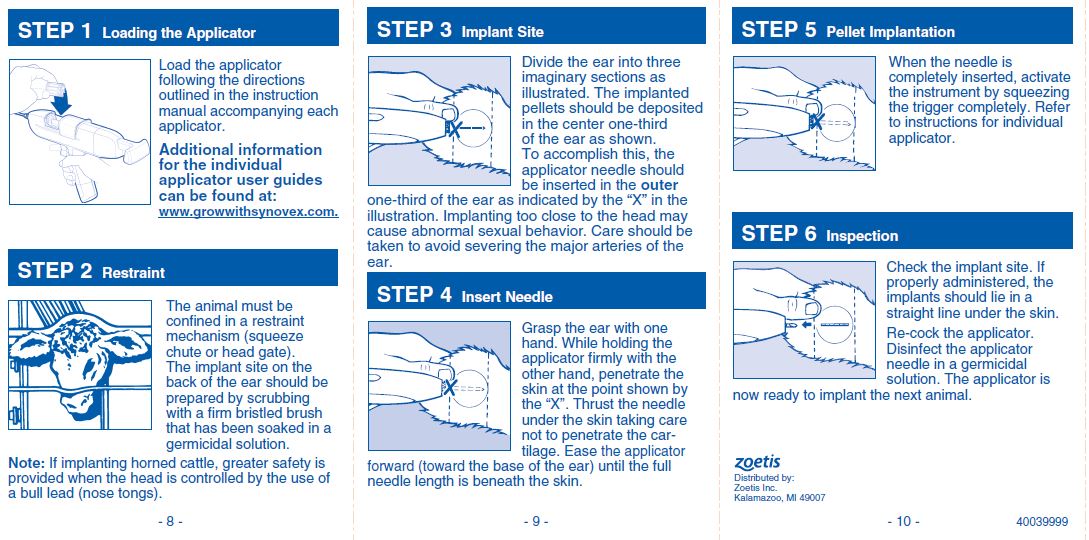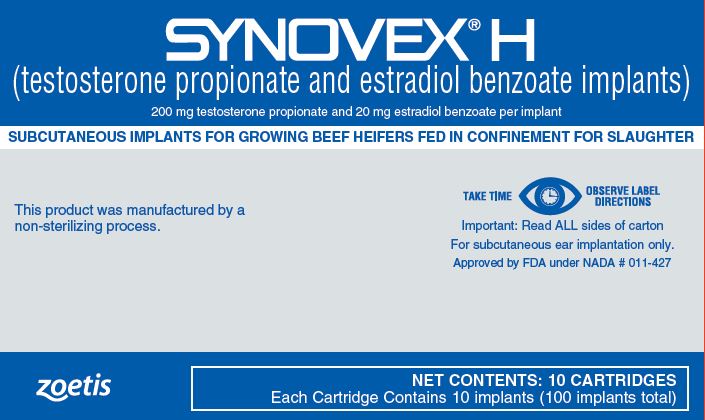 DRUG LABEL: Synovex H
NDC: 54771-3901 | Form: IMPLANT
Manufacturer: Zoetis Inc.
Category: animal | Type: OTC ANIMAL DRUG LABEL
Date: 20230706

ACTIVE INGREDIENTS: TESTOSTERONE PROPIONATE 200 mg/1 1; ESTRADIOL BENZOATE 20 mg/1 1

Synovex H

Synovex® H

(testosterone propionate and estradiol benzoate implants)
200 mg testosterone propionate and 20 mg estradiol benzoate per implant
SUBCUTANEOUS IMPLANTS FOR GROWING BEEF HEIFERS FED IN CONFINEMENT FOR SLAUGHTER
This product was manufactured by a non-sterilizing process.
TAKE TIME OBSERVE LABEL DIRECTIONS
Important: Read ALL sides of carton
For subcutaneous ear implantation only.
Approved by FDA under NADA # 011-427

NET CONTENTS: 10 CARTRIDGES
Each Cartridge Contains 10 implants (100 implants total)

Restricted Drug (California) — Use Only as Directed

WITHDRAWAL PERIODS AND RESIDUE WARNINGS

No withdrawal period is required when used according to labeling. Do not use in beef calves less than 2 months of age, dairy calves, and veal calves. A withdrawal period has not been established for this product in pre-ruminating calves. Do not use in dairy cows or in animals intended for subsequent breeding. Use in these cattle may cause drug residues in milk and/or in calves born to these cows. Implant pellets subcutaneously in ear only. Any other location is a violation of Federal Law.
Do not attempt salvage of implanted site for human or animal food.

USER SAFETY WARNINGS

Not for use in humans. Keep out of reach of children.

ANIMAL SAFETY WARNINGS

Bulling has occasionally been reported in implanted steers and heifers. Vaginal and rectal prolapse, udder development, ventral edema and elevated tailheads have occasionally been reported in heifers administered SYNOVEX® H implants.

INDICATIONS FOR USE

· For increased rate of weight gain and improved feed efficiency in growing beef heifers fed in confinement for slaughter.
· Other than as described on the labeling, this implant is not approved for repeated implantation (reimplantation) with any other cattle ear implant in growing beef heifers fed in confinement for slaughter as safety and effectiveness have not been evaluated.
Do not use in beef calves less than 2 months of age, dairy calves, and veal calves because effectiveness and safety have not been evaluated.
Do not use in animals intended for subsequent breeding, or in dairy cows.

Dosage

Implant complete contents of one cartridge cell per heifer. Approved implantation technique is fully described in the package insert.

NOTE: Never sacrifice careful, clean technique for speed of implantation.

DIRECTIONS

Implant complete contents of one cartridge cell per heifer. Approved implantation technique is fully described in the package insert.
NOTE: Never sacrifice careful, clean technique for speed of implantation.

Storage

Store at controlled room temperature 20°-25°C (68°-77°F) with excursions between 15°-30°C (59°-86°F). Avoid excessive heat or humidity.

HOW SUPPLIED

100 Dose

QUESTIONS/COMMENTS?

For a copy of the Safety Data Sheet or to report side effects, contact Zoetis Inc. at 1-888-963-8471. For additional information about reporting side effects for animal drugs, contact FDA at 1-888-FDA-VETS or http://www.fda.gov/reportanimalae.

Distributed by:
Zoetis Inc.
Kalamazoo, MI 49007
Revised: May 2023
40039999

PRINCIPAL DISPLAY PANEL - Carton of 10 cartridges

40039999